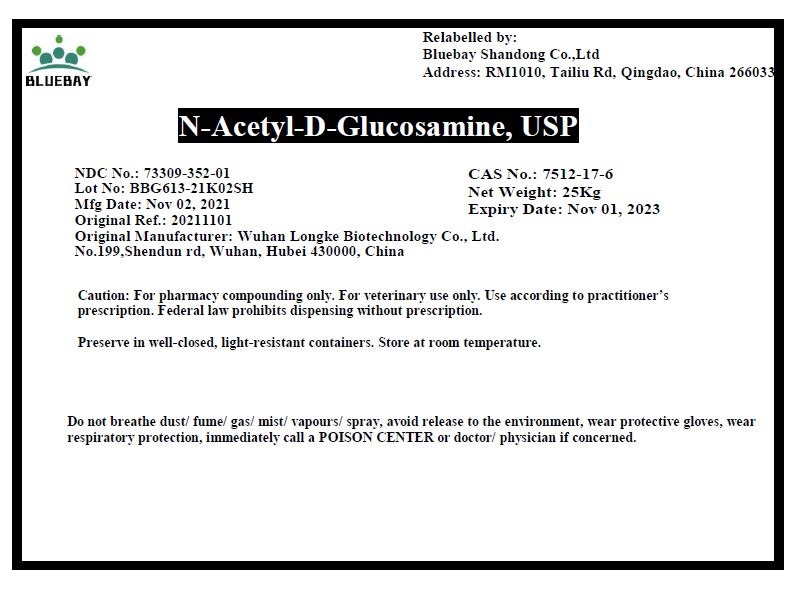 DRUG LABEL: N-Acetyl-D-Glucosamine
NDC: 73309-352 | Form: POWDER
Manufacturer: BLUEBAY SHANDONG CO.,LTD
Category: other | Type: BULK INGREDIENT
Date: 20211130

ACTIVE INGREDIENTS: N-ACETYLGLUCOSAMINE 1 kg/1 kg

N-Acetyl-D-Glucosamine